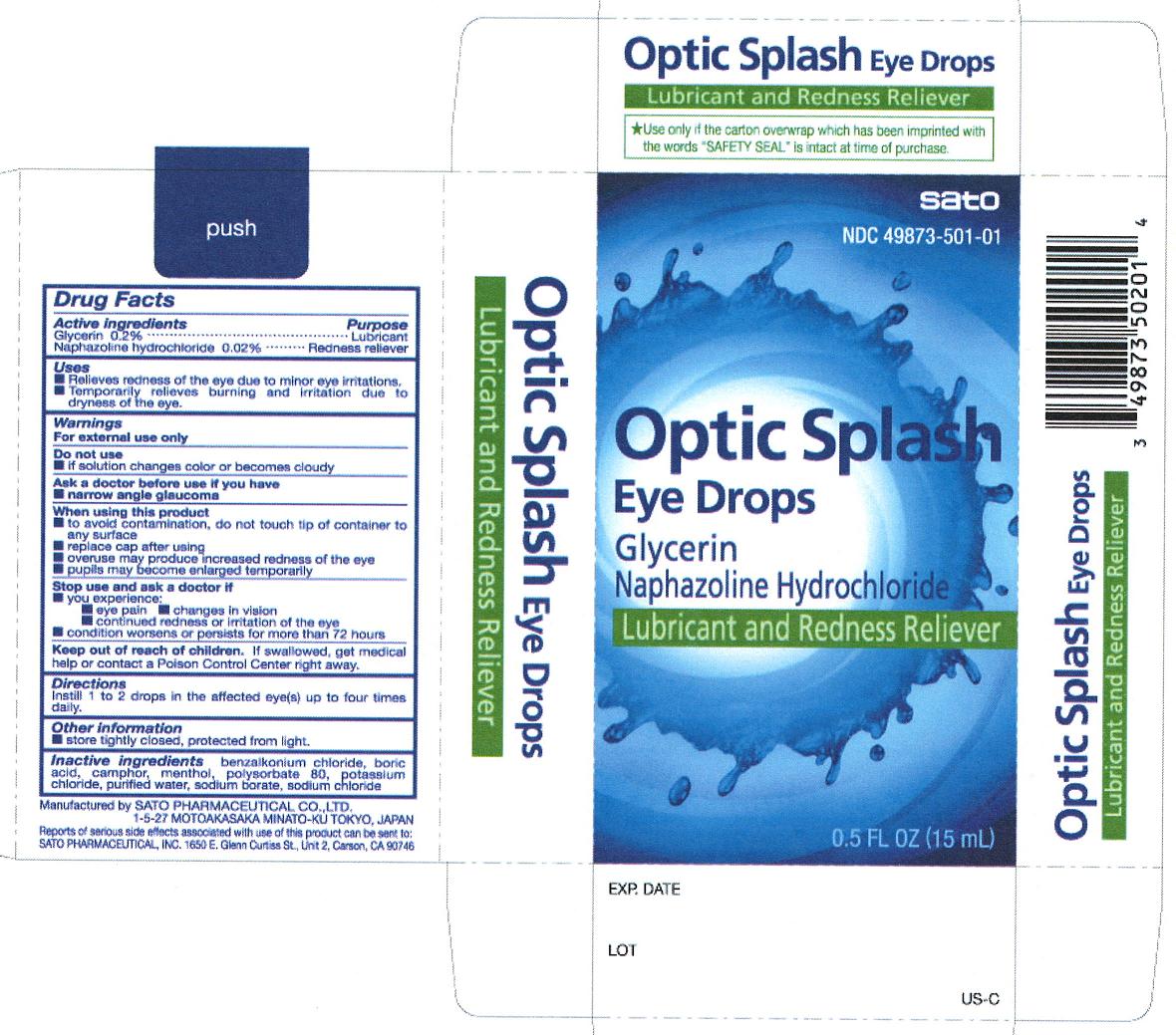 DRUG LABEL: Optic Splash
NDC: 49873-501 | Form: SOLUTION/ DROPS
Manufacturer: Sato Pharmaceutical, Co., Ltd.
Category: otc | Type: HUMAN OTC DRUG LABEL
Date: 20231204

ACTIVE INGREDIENTS: NAPHAZOLINE HYDROCHLORIDE 20 mg/100 mL; GLYCERIN 200 mg/100 mL
INACTIVE INGREDIENTS: BORIC ACID; CAMPHOR (SYNTHETIC); BENZALKONIUM CHLORIDE; LEVOMENTHOL; POLYSORBATE 80; POTASSIUM CHLORIDE; SODIUM BORATE; SODIUM CHLORIDE; WATER

Optic Splash

Active ingredients
Glycerin 0.2%
Naphazoline hydrochloride 0.02%

Purpose
Glycerin Lubricant
Naphazoline hydrochloride Redness reliever

Uses
■ Relieves redness of the eye due to minor eye irritations.
■ Temporarily relieves burning and irritation due to dryness of the eye.

Warnings
For external use only

Do not use
■ if solution changes color or becomes cloudy

ASK DOCTOR

A sk a doctor before use if you have
■ narrow angle glaucoma

When using this product
■ to avoid contamination, do not touch tip of container to any surface
■ replace cap after using
■ overuse of this product may produce increased redness of the eye
■ pupils may become enlarged temporarily

Stop use and ask a doctor if
■ you experience:
■ eye pain ■ changes in vision
■ continued redness or irritation of the eye
■ condition worsens or persists for more than 72 hours

Keep out of reach of children. If swallowed, get medical help or contact a Poison Control Center right away.

Directions
Instill 1 to 2 drops in the affected eye(s) up to four times daily.

Other information
■ store tightly closed, protected from light.

Inactive ingredients
benzalkonium chloride, boric acid, camphor, menthol, polysorbate 80, potassium chloride, purified water, sodium borate, sodium chloride

PACKAGE LABEL

opticsplashcart.jpg